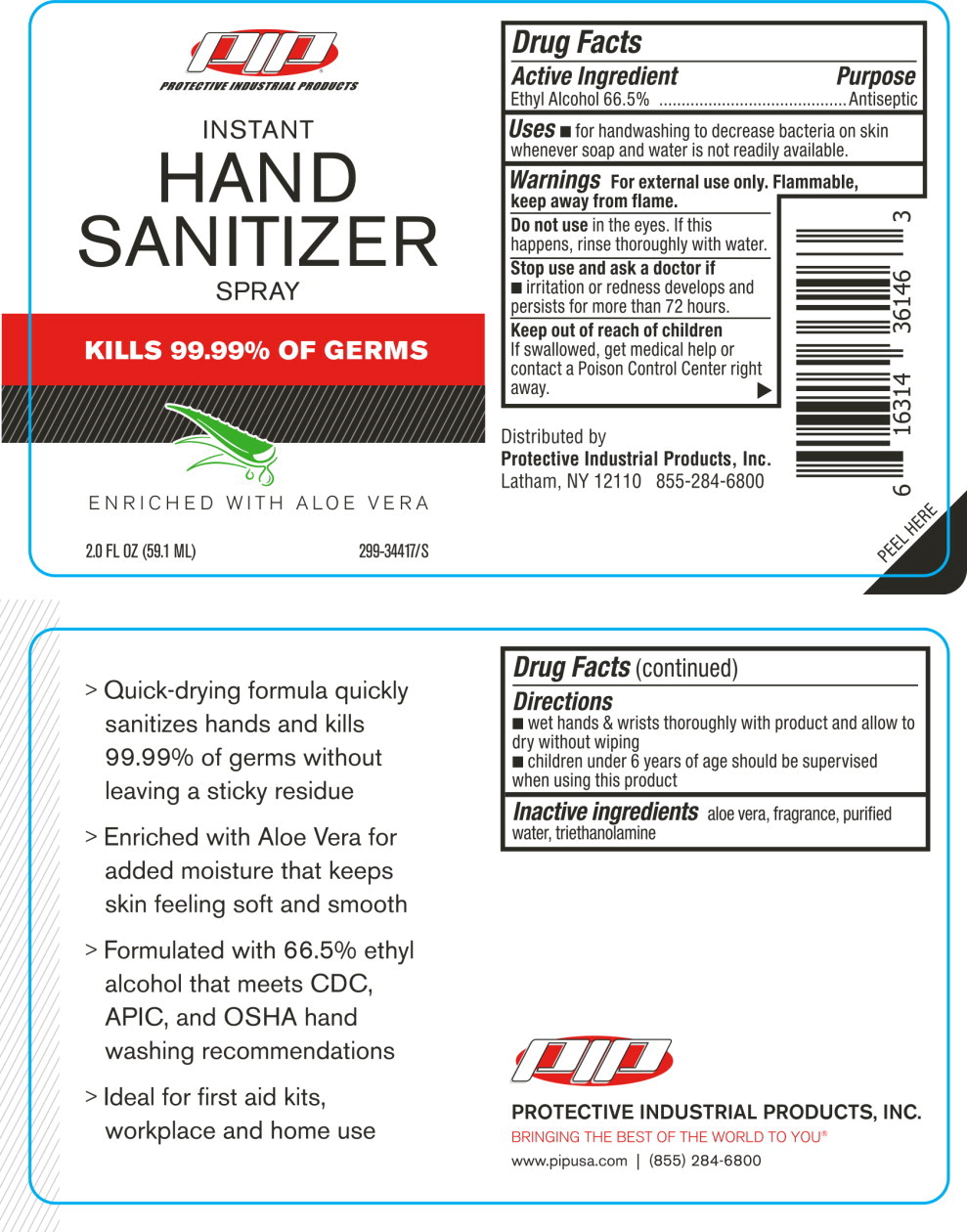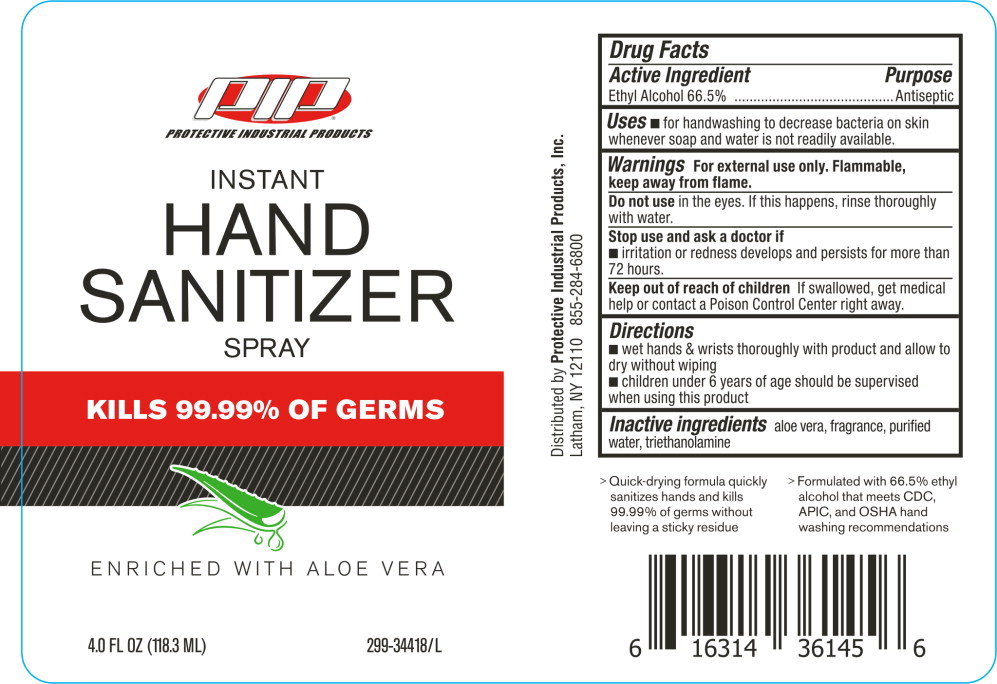 DRUG LABEL: Protective Industrial Products Instant Hand Sanitizer
NDC: 80716-299 | Form: SPRAY
Manufacturer: Protective Industrial Products
Category: otc | Type: HUMAN OTC DRUG LABEL
Date: 20201006

ACTIVE INGREDIENTS: ALCOHOL 0.665 mL/1 mL
INACTIVE INGREDIENTS: ALOE VERA LEAF; WATER; TROLAMINE

Drug Facts

Active Ingredient

Ethyl Alcohol 66.5%

Purpose

Antiseptic

Uses

- for handwashing to decrease bacteria on skin whenever soap and water is not readily available.

Warnings

For external use only. Flammable, keep away from flame.

Do not use in the eyes. If this happens, rinse thoroughly with water.

Stop use and ask a doctor if

- irritation or redness develops and persists for more than 72 hours.

Keep out of reach of children

If swallowed, get medical help or contact a Poison Control Center right away.

Directions

- wet hands & wrists thoroughly with product and allow to dry without wiping
- children under 6 years of age should be supervised when using this product

Inactive ingredients

aloe vera, fragrance, purified triethanolamine

Principal Display Panel - 2.0 FL OZ Bottle Label

PIP®

PROTECTIVE INDUSTRIAL PRODUCTS

INSTANT
HAND
SANITIZER
SPRAY

KILLS 99.99% OF GERMS

ENRICHED WITH ALOE VERA

2.0 FL OZ (59.1 ML)

299-34417/S

Principal Display Panel - 4.0 FL OZ Bottle Label

PIP®

PROTECTIVE INDUSTRIAL PRODUCTS

INSTANT
HAND
SANITIZER
SPRAY

KILLS 99.99% OF GERMS

ENRICHED WITH ALOE VERA

4.0 FL OZ (118.3 ML)

299-34418/S